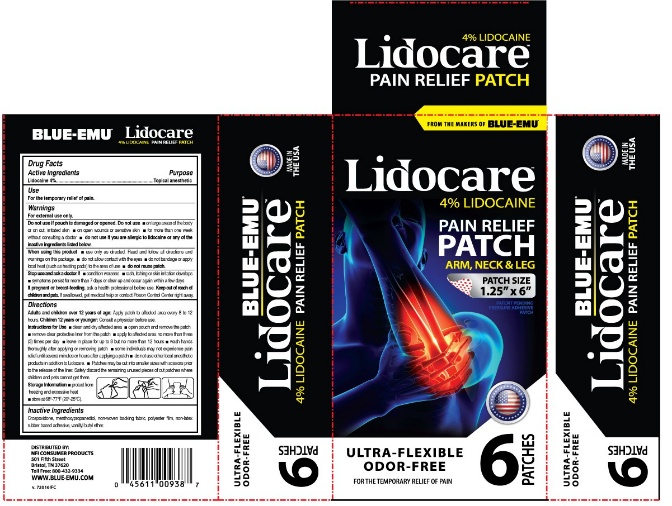 DRUG LABEL: Lidocare Arm, Neck, Leg
NDC: 69993-450 | Form: PATCH
Manufacturer: Kingsway Pharmaceuticals dba NFI, LLC
Category: otc | Type: HUMAN OTC DRUG LABEL
Date: 20250106

ACTIVE INGREDIENTS: LIDOCAINE 11 mg/1 1
INACTIVE INGREDIENTS: CROSPOVIDONE, UNSPECIFIED; 3-(L-MENTHOXY)-2-METHYLPROPANE-1,2-DIOL; VANILLYL BUTYL ETHER

Lidocare™ Arm, Neck, Leg Patch

Active Ingredients

Lidocaine 4%

Purpose

Topical anesthetic

Use

For the temporary relief of pain.

Warnings

For external use only.

Do not use if pouch is damaged or opened. Do not use

- on large areas of the body or on cut, irritated skin
- on open wounds or sensitive skin
- for more than one week without consulting a doctor
- do not use if you are allergic to lidocaine or any of the inactive ingredients listed below.

When using this product

- use only as directed. Read and follow all directions and warnings on this package.
- do not allow contact with the eyes
- do not bandage or apply local heat (such as heating pads) to the area of use
- do not reuse patch.

Stop use and ask doctor if

- condition worsens
- rash, itching or skin irritation develops
- symptoms persist for more than 7 days or clear up and occur again within a few days

If pregnant or breast feeding,

ask a health professional before use.

Keep out of reach of children and pets.

If swallowed, get medical help or contact Poison Control Center right away.

Directions

Adults and children over 12 years of age: Apply patch to affected area every 8 to 12 hours.
Children 12 years or younger: Consult a physician before use.

Instructions for Use

- clean and dry affected area
- open pouch and remove the patch
- remove clear protective liner from the patch
- apply to affected area no more than three (3) times per day
- leave in place for up to 8 but no more than 12 hours
- wash hands thoroughly after applying or removing patch
- some individuals may not experience pain relief until several minutes or hours after applying a patch
- do not use other local anesthetic products in addition to Lidocare.
- Patches may be cut into smaller sizes with scissors prior to the release of the liner. Safely discard the remaining unused pieces of cut patches where children and pets cannot get them.

Storage Information

- protect from freezing or excessive heat
- store at 68°-77°F (20°-25°C).

Inactive Ingredients

Crospovidone, menthoxypropanediol, non-woven backing fabric, polyester film, non-latex rubber based adhesive, vanillyl butyl ether.

DISTRIBUTED BY:
NFI CONSUMER PRODUCTS
501 Fifth Street
Bristol, TN 37620
Toll Free: 800-432-9334
WWW.BLUE-EMU.COM

PRINCIPAL DISPLAY PANEL – 6 Patch Carton Label

FROM THE MAKERS OF BLUE-EMU®
Lidocare™
4% LIDOCAINE
PAIN RELIEF
PATCH
ARM, NECK & LEG
PATCH SIZE
1.25” x 6”
PATENT PENDING
PRESSURE ADHESIVE
PATCH

ULTRA-FLEXIBLE
ODOR-FREE
FOR THE TEMPORARY RELIEF OF PAIN
6 PATCHES